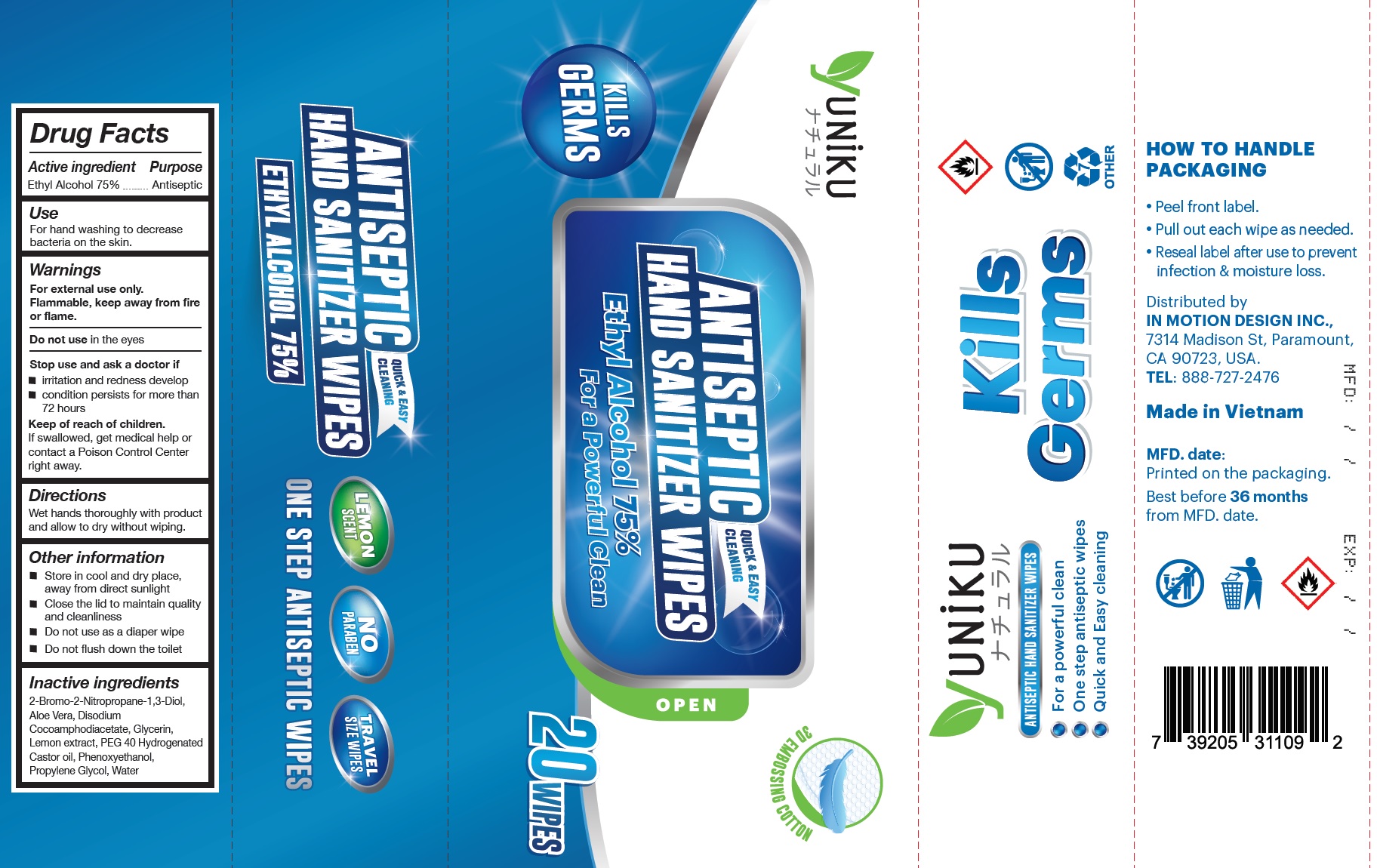 DRUG LABEL: Antiseptic Hand Sanitizer Wipes
NDC: 78898-000 | Form: PATCH
Manufacturer: Eco Wipes Vietnam Corporation
Category: otc | Type: HUMAN OTC DRUG LABEL
Date: 20200702

ACTIVE INGREDIENTS: ALCOHOL 0.75 mL/1 mL
INACTIVE INGREDIENTS: BRONOPOL; ALOE VERA LEAF; DISODIUM COCOAMPHODIACETATE; GLYCERIN; LEMON; POLYOXYL 40 HYDROGENATED CASTOR OIL; PHENOXYETHANOL; PROPYLENE GLYCOL; WATER

Antiseptic Hand Sanitizer Wipes

Active ingredient

Ethyl Alcohol 75%

Purpose

Antiseptic

Use

For hand washing to decrease bacteria on the skin.

Warnings

For external use only.
Flammable, keep away from fire or flame.

Do not use

in the eyes

Stop use and ask a doctor if

- irritation and redness develop
- condition persists for more than 72 hours

Keep of reach of children.

If swallowed, get medical help or contact a Poison Control Center right away.

Directions

Wet hands thoroughly with product and allow to dry without wiping.

Other information

- Store in cool and dry place, away from direct sunlight
- Close the lid to maintain quality and cleanliness
- Do not use as a diaper wipe
- Do not flush down the toilet

Inactive ingredients

2-Bromo-2-Nitropropane-1,3-Diol, Aloe Vera, Disodium Cocoamphodiacetate, Glycerin, Lemon extract, PEG 40 Hydrogenated Castor oil, Phenoxyethanol, Propylene Glycol, Water